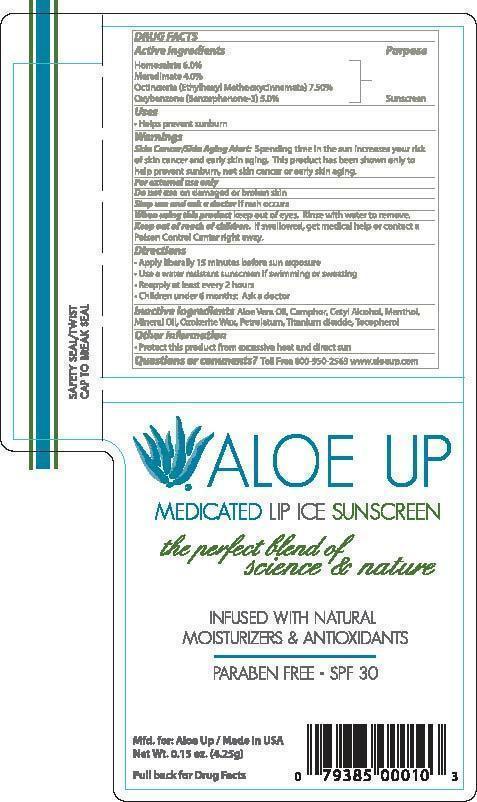 DRUG LABEL: ALOE UP MEDICATED LIP ICE SUNSCREEN
NDC: 61477-215 | Form: LIPSTICK
Manufacturer: Aloe Care International, LLC
Category: otc | Type: HUMAN OTC DRUG LABEL
Date: 20240213

ACTIVE INGREDIENTS: OCTINOXATE 7.5 g/100 g; HOMOSALATE 6 g/100 g; MERADIMATE 4 g/100 g; OXYBENZONE 5 g/100 g
INACTIVE INGREDIENTS: ALOE VERA LEAF; CAMPHOR (SYNTHETIC); CETYL ALCOHOL; MENTHOL; MINERAL OIL; CERESIN; PETROLATUM; TITANIUM DIOXIDE; TOCOPHEROL

ALOE UP - MEDICATED LIP ICE SUNSCREEN SPF-30 (61477-215)

ACTIVE INGREDIENTS:

HOMOSALATE (6%)

MERADIMATE (4%)

OCTINOXATE (7.5%)

OXYBENZONE (4.5%)

PURPOSE:

SUNSCREEN

USES

HELPS PREVENT SUNBURN.

DIRECTIONS:

APPLY LIBERALLY 15 MINUTES BEFORE SUN EXPOSURE.

USE A WATER RESISTANT SUNSCREEN IF SWIMMING OR SWEATING.

REAPPLY AT LEAST EVERY 2 HOURS.

CHILDREN UNDER 6 MONTHS: ASK A DOCTOR.

KEEP OUT OF REACH OF CHILDREN. IF SWALLOWED, GET MEDICAL HELP OR CONTACT A POISON CONTROL CENTER RIGHT AWAY.

WARNINGS:

Skin Cancer/Skin Aging Alert: Spending time in the sun increases your risk of skin cancer and early skin aging. This product has been shown only to help prevent sunburn, not skin cancer or early skin aging.
For external use only
Do not use on damaged or broken skin
Stop use and ask a doctor if rash occurs
When using this product keep out of eyes. Rinse with water to remove.

INACTIVE INGREDIENTS

ALOE VERA OIL, CAMPHOR, CETYL ALCOHOL, MENTHOL, MINERAL OIL, OZOKERITE WAX, PETROLATUM, TITANIUM DIOXIDE, TOCOPHEROL

OTHER INFORMATION

• Protect this product from excessive heat and direct sun

Questions or comments?

Toll Free 800-950-2563 www.aloeup.com